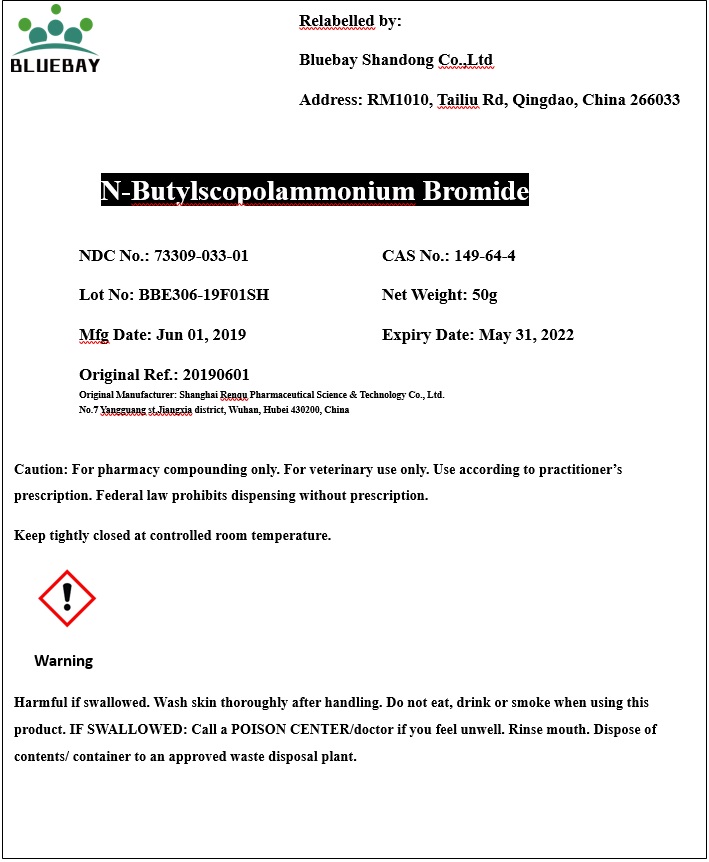 DRUG LABEL: n-Butylscopolammonium Bromide
NDC: 73309-033 | Form: POWDER
Manufacturer: BLUEBAY SHANDONG CO.,LTD
Category: other | Type: BULK INGREDIENT
Date: 20190912

ACTIVE INGREDIENTS: BUTYLSCOPOLAMINE BROMIDE 1 g/1 g

n-Butylscopolammonium Bromide